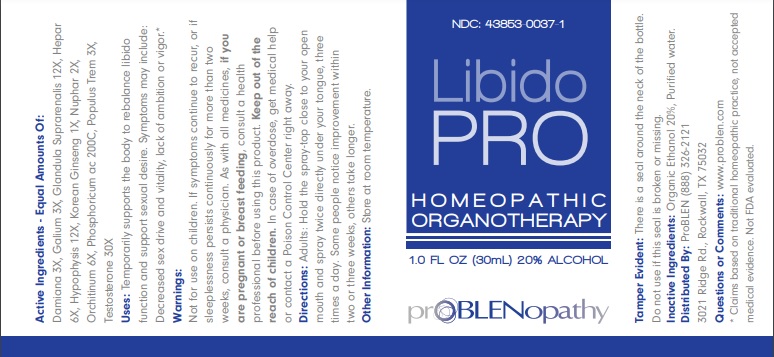 DRUG LABEL: LIBIDOPRO
NDC: 43853-0037 | Form: LIQUID
Manufacturer: ProBlen
Category: homeopathic | Type: HUMAN OTC DRUG LABEL
Date: 20221130
DEA Schedule: CIII

ACTIVE INGREDIENTS: TURNERA DIFFUSA LEAFY TWIG 3 [hp_X]/30 mL; GALLIUM 3 [hp_X]/30 mL; SUS SCROFA ADRENAL GLAND 12 [hp_X]/30 mL; PORK LIVER 6 [hp_X]/30 mL; SUS SCROFA PITUITARY GLAND 12 [hp_X]/30 mL; ASIAN GINSENG 1 [hp_X]/30 mL; NUPHAR LUTEA LEAF 2 [hp_X]/30 mL; BOS TAURUS TESTICLE 2 [hp_X]/30 mL; PHOSPHORIC ACID 200 [hp_C]/30 mL; POPULUS TREMULA FLOWERING TOP 3 [hp_X]/30 mL; TESTOSTERONE 30 [hp_X]/30 mL
INACTIVE INGREDIENTS: ALCOHOL; WATER

LibidoPRO

ACTIVE INGREDIENT

Active Ingredients - Equal Amounts Of: Damiana 3X, Galium 3X, Glandula Suprarenalis 12X, Hepar 6X, Hypophysis 12X, Korean Ginseng 1X, Nuphar 2X, Orchitinum 6X, Phosphoricum ac 200C, Populus Trem 3X, Testosterone 30X

* Claims based on traditional homeopathic practice, not accepted medical evidence. Not FDA evaluated.

INDICATIONS AND USAGE

Uses: Temporarily supports the body to rebalance libido function and support sexual desire. Symptoms may include: Decreased sex drive and vitality, lack of ambition or vigor.*

WARNINGS

Warnings: Not for use on children. If symptoms continue to recur, or if sleeplessness persists continuously for more than two weeks, consult a physician. As with all medicines, if you are pregnant or breast feeding, consult a health professional before using this product. Keep out of the
reach of children. In case of overdose, get medical help or contact a Poison Control Center right away.

Keep out of the reach of children.

DOSAGE AND ADMINISTRATION

Directions: Adults: Hold the spray-top close to your open mouth and spray twice directly under your tongue, three times a day. Some people notice improvement within two or three weeks, others take longer.

Other Information: Store at room temperature

Tamper Evident: There is a seal around the neck of the bottle. Do not use if this seal is broken or missing.

Inactive Ingredients: Organic Ethanol 20%, Purified water.

QUESTIONS

Distributed By: ProBLEN (888) 326-2121
3021 Ridge Rd., Rockwall, TX 75032

Questions or Comments: www.problen.com

PACKAGE LABEL

NDC: 43853-0037-1

LibidoPRO

HOMEOPATHIC ORGANOTHERAPY

1.0 FL OZ (30mL) 20% ALCOHOL

PURPOSE

Purpose: Temporarily supports the body to rebalance libido function and support sexual desire. Symptoms may include: Decreased sex drive and vitality, lack of ambition or vigor.